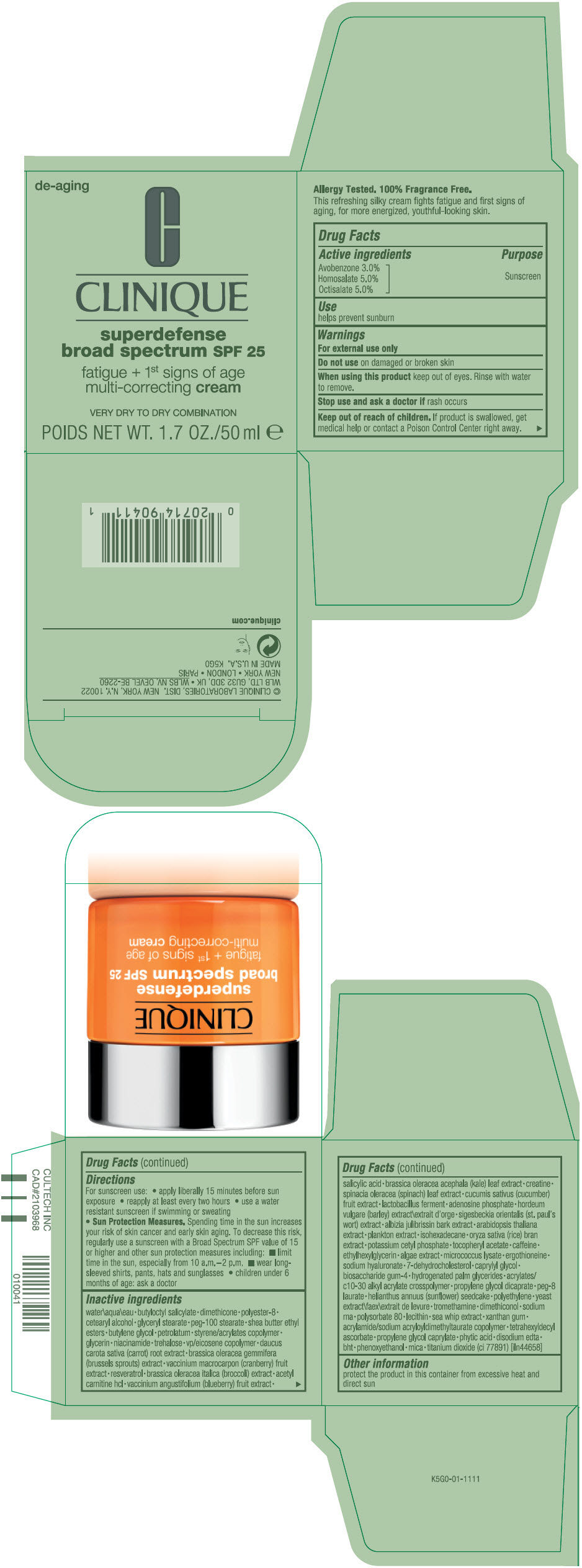 DRUG LABEL: SUPERDEFENSE BROAD SPECTRUM SPF 25 FATIGUE PLUS 1ST SIGNS OF AGE MULTI-CORRECTING VERY DRY TO DRY COMBINATION
NDC: 49527-077 | Form: CREAM
Manufacturer: CLINIQUE LABORATORIES LLC
Category: otc | Type: HUMAN OTC DRUG LABEL
Date: 20231019

ACTIVE INGREDIENTS: AVOBENZONE 30 mg/1 mL; HOMOSALATE 50 mg/1 mL; OCTISALATE 50 mg/1 mL
INACTIVE INGREDIENTS: RICE BRAN; POTASSIUM CETYL PHOSPHATE; .ALPHA.-TOCOPHEROL ACETATE; CAFFEINE; ETHYLHEXYLGLYCERIN; ERGOTHIONEINE; HYALURONATE SODIUM; 7-DEHYDROCHOLESTEROL; CAPRYLYL GLYCOL; BIOSACCHARIDE GUM-4; WATER; BUTYLOCTYL SALICYLATE; DIMETHICONE; POLYESTER-8 (1400 MW, CYANODIPHENYLPROPENOYL CAPPED); CETOSTEARYL ALCOHOL; GLYCERYL MONOSTEARATE; PEG-100 STEARATE; BUTYLENE GLYCOL; PETROLATUM; STYRENE/ACRYLAMIDE COPOLYMER (500000 MW); GLYCERIN; NIACINAMIDE; TREHALOSE; CARROT; BRUSSELS SPROUT; CRANBERRY; RESVERATROL; BROCCOLI; LEVACECARNINE HYDROCHLORIDE; LOWBUSH BLUEBERRY; SALICYLIC ACID; KALE; CREATINE; SPINACH; CUCUMBER; ADENOSINE PHOSPHATE; BARLEY; ALBIZIA JULIBRISSIN BARK; ARABIDOPSIS THALIANA WHOLE; ISOHEXADECANE; HYDROGENATED PALM GLYCERIDES; CARBOMER INTERPOLYMER TYPE A (ALLYL SUCROSE CROSSLINKED); PROPYLENE GLYCOL DICAPRATE; PEG-8 LAURATE; HELIANTHUS ANNUUS SEEDCAKE; HIGH DENSITY POLYETHYLENE; TROMETHAMINE; POLYSORBATE 80; PSEUDOPTEROGORGIA ELISABETHAE; XANTHAN GUM; TETRAHEXYLDECYL ASCORBATE; PROPYLENE GLYCOL MONOCAPRYLATE; FYTIC ACID; EDETATE DISODIUM ANHYDROUS; BUTYLATED HYDROXYTOLUENE; PHENOXYETHANOL; MICA; TITANIUM DIOXIDE

SUPERDEFENSE BROAD SPECTRUM SPF 25 FATIGUE + 1ST SIGNS OF AGE MULTI-CORRECTING VERY DRY TO DRY COMBINATION

Drug Facts

Active ingredients

Avobenzone 3.0%
Homosalate 5.0%
Octisalate 5.0%

Purpose

Sunscreen

Use

helps prevent sunburn

Warnings

For external use only

Do not use on damaged or broken skin

When using this product keep out of eyes. Rinse with water to remove.

Stop use and ask a doctor if rash occurs

Keep out of reach of children. If product is swallowed, get medical help or contact a Poison Control Center right away.

Directions

For sunscreen use:

- apply liberally 15 minutes before sun exposure
- reapply at least every two hours
- use a water resistant sunscreen if swimming or sweating
- Sun Protection Measures. Spending time in the sun increases your risk of skin cancer and early skin aging. To decrease this risk, regularly use a sunscreen with a Broad Spectrum SPF value of 15 or higher and other sun protection measures including:
  - limit time in the sun, especially from 10 a.m.–2 p.m.
  - wear long-sleeved shirts, pants, hats and sunglasses
- children under 6 months of age: ask a doctor

Inactive ingredients

water\aqua\eau • butyloctyl salicylate • dimethicone • polyester-8 • cetearyl alcohol • glyceryl stearate • peg-100 stearate • shea butter ethyl esters • butylene glycol • petrolatum • styrene/acrylates copolymer • glycerin • niacinamide • trehalose • vp/eicosene copolymer • daucus carota sative (carrot) root extract • brassica oleracea gemmifera (brussels sprouts) extract • vaccinium macrocarpon (cranberry) fruit extract • resveratrol • brassica oleracea italica (broccoli) extract • acetyl carnitine hcl • vaccinium angustifolium (blueberry) fruit extract • salicylic acid • brassica oleracea acephala (kale) leaf extract • creatine • spinacia oleracea (spinach) leaf extract • cucumis sativus (cucumber) fruit extract • lactobacillus ferment • adenosine phosphate • hordeum vulgare (barley) extract\extrait d'orge • sigesbeckia orientalis (st. paul's wort) extract • albizia julibrissin bark extract • arabidopsis thaliana extract • plankton extract • isohexadecane • oryza sativa (rice) bran extract • potassium cetyl phosphate • tocopheryl acetate • caffeine • ethylhexylglycerin • algae extract • micrococcus lysate • ergothioneine • sodium hyaluronate • 7-dehydrocholesterol • caprylyl glycol • biosaccharide gum-4 • hydrogenated palm glycerides • acrylates/c10-30 alkyl acrylate crosspolymer • propylene glycol dicaprate • peg-8 laurate • helianthus annuus (sunflower) seedcake • polyethylene • yeast extract\faex\extrait de levure • tromethamine • dimethiconol • sodium rna • polysorbate 80 • lecithin • sea whip extract • xanthan gum • acrylamide/sodium acryloyldimethyltaurate copolymer • tetrahexyldecyl ascorbate • propylene glycol caprylate • phytic acid • disodium edta • bht • phenoxyethanol • mica • titanium dioxide (ci 77891) [iln44658]

Other information

protect the product in this container from excessive heat and direct sun

PRINCIPAL DISPLAY PANEL - 50 ml Jar Carton

de-aging

CLINIQUE

superdefense
broad spectrum SPF 25

fatigue + 1st signs of age
multi-correcting cream

VERY DRY TO DRY COMBINATION

NET WT. 1.7 OZ./50 ml e